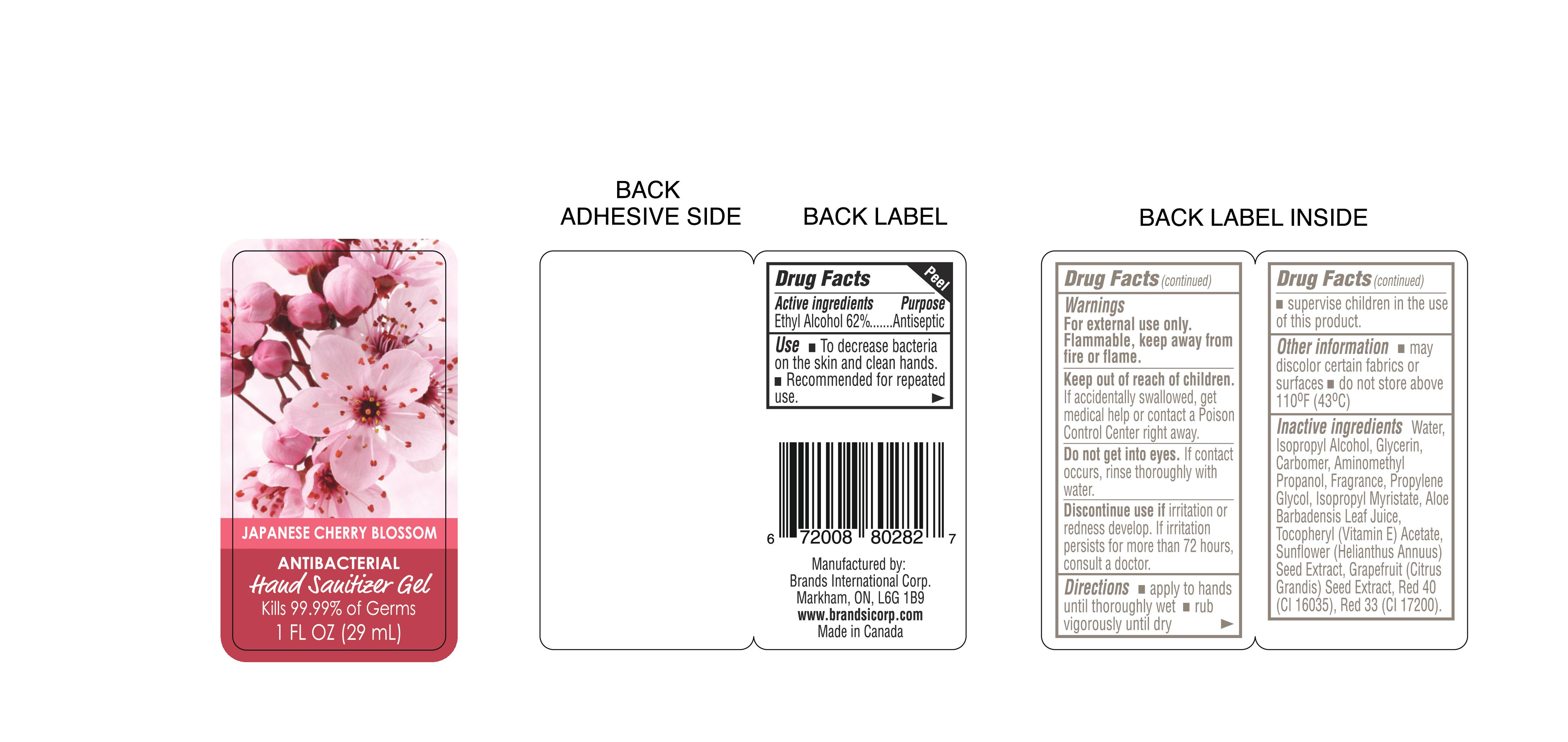 DRUG LABEL: Japanese Cherry Blossom
NDC: 50157-115 | Form: GEL
Manufacturer: Brands International Corp
Category: otc | Type: HUMAN OTC DRUG LABEL
Date: 20161023

ACTIVE INGREDIENTS: ALCOHOL 620 mL/1000 mL
INACTIVE INGREDIENTS: GLYCERIN; CARBOMER 940; AMINOMETHYLPROPANOL; PROPYLENE GLYCOL; .ALPHA.-TOCOPHEROL ACETATE; FD&C RED NO. 40; GRAPEFRUIT SEED OIL; WATER; ISOPROPYL ALCOHOL; ISOPROPYL MYRISTATE; ALOE VERA LEAF; SUNFLOWER SEED

ACTIVE INGREDIENT

Ethyl Alcohol 62%

Purpose - Antiseptic

Use

- To decrease bacteria on the skin and clean hands
- recommened for repeated use

Warnings

For external use only

Flammable, Keep away from fire or flame

Keep out of children

If accidently swallowed, get medical help or contact a Poison Control Center right away

USER SAFETY WARNINGS

Do not get into eyes

If contact occurs, rinse thoroughly with water

ASK DOCTOR/PHARMACIST

Discontinue use if irritation or redness develop. If irritation persists for more than 72 hrs, consult a doctor

Directions

- apply to hands until thoroughly wet
- rub vigorously unti dry
- supervise children in the use of this product

Other Information

- May discolor certain fabrics or surfaces
- do not store above 110 F (43 C)

INACTIVE INGREDIENT

Water, Isopropyl Alcohol, Glycerin, Carbomer, Aminomethyl Propanol, Fragrance, Proylene glycol, Isopropyl Myristate, Aloe Barbadensis Leaf Juice, Tocopheryl (Vitamin E) Actetate, Sunflower (Helianthus Annuus) Seed Extract, Grapefruit (Citrus Grandis), Seed Extract, Red 40 (Cl 16035), Red 33 (Cl 17200)